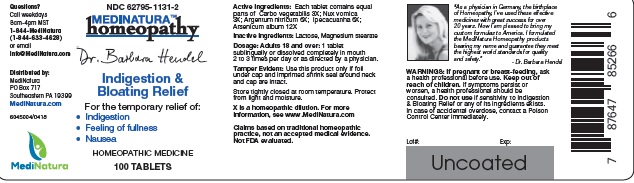 DRUG LABEL: Hendel Indigestion and Bloating
NDC: 62795-1131 | Form: TABLET
Manufacturer: MediNatura Inc
Category: homeopathic | Type: HUMAN OTC DRUG LABEL
Date: 20220822

ACTIVE INGREDIENTS: ACTIVATED CHARCOAL 3 [hp_X]/1 1; STRYCHNOS NUX-VOMICA SEED 3 [hp_X]/1 1; SILVER NITRATE 6 [hp_X]/1 1; ARSENIC TRIOXIDE 12 [hp_X]/1 1; IPECAC 6 [hp_X]/1 1
INACTIVE INGREDIENTS: LACTOSE MONOHYDRATE; MAGNESIUM STEARATE

Hendel Indigestion and Bloating

WARNINGS

If pregnant or breast-feeding, ask a health professional before use. Keep out of reach of children. If symptoms persist or worsen, a health professional should be consulted. Do not use if sensitivity to Indigestion & Bloating Relief or any of its ingredients exists. In case of accidental overdose, contact a Poison
Control Center immediately.

KEEP OUT OF REACH OF CHILDREN

USES

Indigestion & Bloating Relief

ACTIVE INGREDIENT

Each tablet contains equal parts of Carbo vegetabilis 3X; Nux vomica 3X; Argentum nitricum 6X; Arsenicum album 12X; Ipecacuanha 6X

INACTIVE INGREDIENT

Lactose, Magnesium stearate

DOSAGE

Adults 18 and over: 1 tablet sublingually or dissolved completely in mouth 2 to 3 times per day or as directed by a physician

USES

For the temporary relief of:
• Indigestion
• Feeling of fullness
• Nausea

PACKAGE LABEL

Add image transcription here...